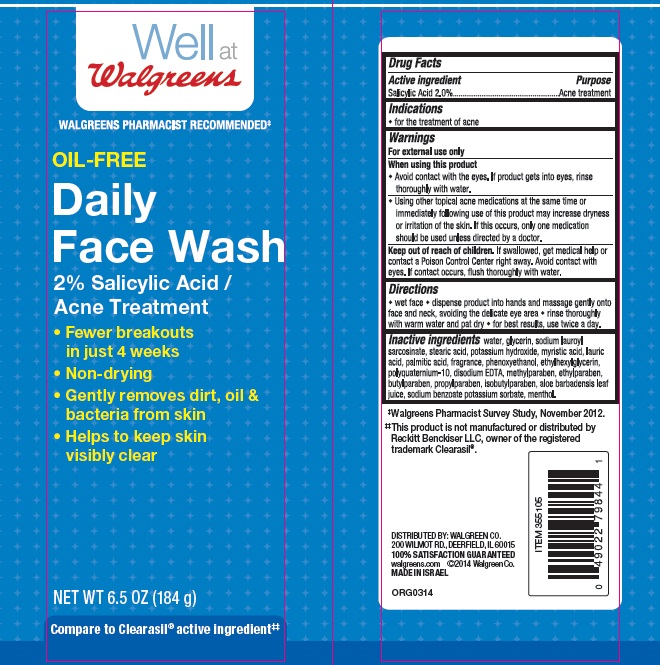 DRUG LABEL: Oil-Free Daily Face
NDC: 0363-0480 | Form: CREAM
Manufacturer: Walgreen Company
Category: otc | Type: HUMAN OTC DRUG LABEL
Date: 20140917

ACTIVE INGREDIENTS: SALICYLIC ACID 2 g/100 g
INACTIVE INGREDIENTS: WATER; GLYCERIN; SODIUM LAUROYL SARCOSINATE; STEARIC ACID; POTASSIUM HYDROXIDE; MYRISTIC ACID; LAURIC ACID; PALMITIC ACID; PHENOXYETHANOL; ETHYLHEXYLGLYCERIN; POLYQUATERNIUM-10 (1000 MPA.S AT 2%); EDETATE DISODIUM; METHYLPARABEN; ETHYLPARABEN; BUTYLPARABEN; PROPYLPARABEN; ISOBUTYLPARABEN; ALOE VERA LEAF; SODIUM BENZOATE; POTASSIUM SORBATE; MENTHOL

Well at Walgreens Oil-Free Daily Face Wash

Active ingredient

Salicylic Acid 2.0%

Purpose

Acne Treatment

Indications

- for the treatment of acne

Warnings

For external use only.

When using this product

- Avoid contact with the eyes. If product gets into eyes, rinse thoroughly with water.
- Using other topical acne medications at the same time or immediately following use of this product may increase dryness or irritation of the skin. If this occurs, only one medication should be used unless directed by a doctor.

Keep Out of Reach of Children.

If swallowed, get medical help or contact a Poison Control Center right away. Avoid contact with eyes. If contact occurs, flush thoroughly with water.

Directions

- wet face
- dispense product into hands and massage gently onto face and neck, avoiding the delicate eye area
- rinse thoroughly with warm water and pat dry
- for best results, use twice a day.

Inactive ingredients

water, glycerin, sodium lauroyl sarcosinate, stearic acid, potassium hydroxide, myristic acid, lauric acid, palmitic acid, fragrance, phenoxyethanol, ethylhexylglycerin, polyquaternium-10, disodium EDTA, methylparaben, ethylparaben, butylparaben, propylparaben, isobutylparaben, aloe barbadensis leaf juice, sodium benzoate potassium sorbate, menthol.

Package/Label Principal Display Panel

Well at
Walgreens

WALGREENS PHARMACIST RECOMMENDED‡

OIL-FREE
Daily
Face Wash

2% Salicylic Acid/
Acne Treatment

- Fewer breakouts
  in just 4 weeks
- Non-drying
- Gently removes dirt, oil &
  bacteria from skin
- Helps to keep skin
  visibly clear

NET WT 6.5 OZ (184 g)

Compare to Clearasil® active ingredient‡‡

‡Walgreens Pharmacist Survey Study, November 2012.

‡‡This product is not manufactured or distributed by Reckitt Benckiser LLC, owner of the registered trademark Clearasil ®.

DISTRIBUTED BY: WALGREEN CO.
200 WILMOT RD., DEERFIELD, IL 60015
100% SATISFACTION GUARANTEED
walgreens.com ©2014 Walgreen Co.
MADE IN ISRAEL

ORG0314

Carton Label